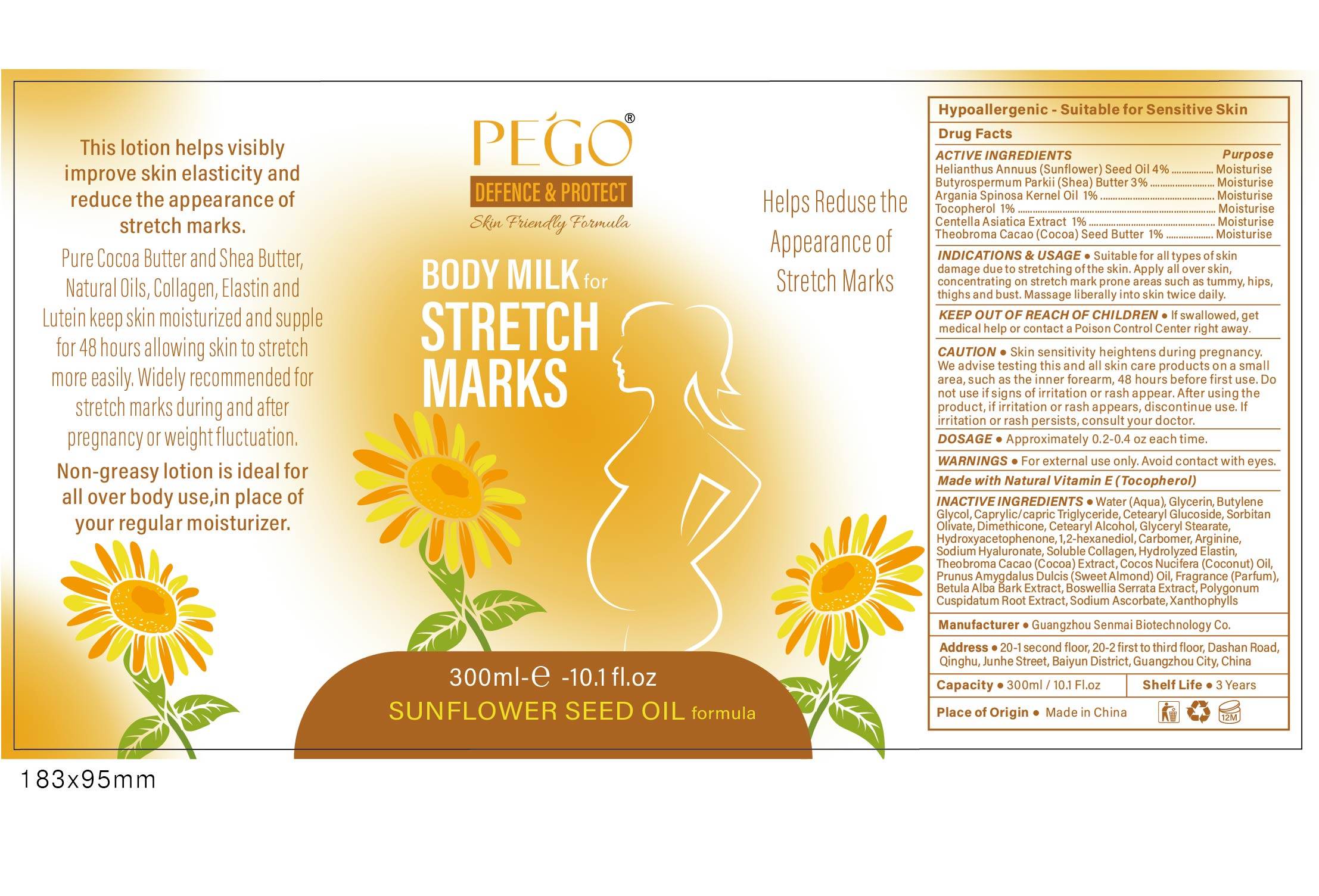 DRUG LABEL: Body Milk for stretch marks
NDC: 84509-004 | Form: LOTION
Manufacturer: Guangzhou Senmai Biotechnology Co.
Category: otc | Type: HUMAN OTC DRUG LABEL
Date: 20250108

ACTIVE INGREDIENTS: SUNFLOWER OIL 12000 mg/300 mL; SHEA BUTTER 9000 mg/300 mL; TOCOPHEROL 3000 mg/300 mL; ARGAN OIL 3000 mg/300 mL; CENTELLA ASIATICA TRITERPENOIDS 3000 mg/300 mL; COCOA BUTTER 3000 mg/300 mL
INACTIVE INGREDIENTS: CETOSTEARYL ALCOHOL; HYALURONATE SODIUM; COLLAGEN, SOLUBLE, FISH SKIN; COCONUT OIL; GLYCERYL MONOSTEARATE; LUTEIN; CARBOMER 1342; SORBITAN OLIVATE; HYDROXYACETOPHENONE; 1,2-HEXANEDIOL; INDIAN FRANKINCENSE; BETULA PUBESCENS BARK; REYNOUTRIA JAPONICA ROOT; GLYCERIN; WATER; BUTYLENE GLYCOL; MEDIUM-CHAIN TRIGLYCERIDES; DIMETHICONE; ARGININE; HYDROLYZED BOVINE ELASTIN (BASE; 1000 MW); COCOA; ALMOND OIL; FRAGRANCE 13576; SODIUM ASCORBATE; CETEARYL GLUCOSIDE

DESCRIPTION

Hypoallergenic-Suitable for Sensitive Skin

Active Ingredients

Helianthus Annuus (Sunflower) Seed Oil 4%

Butyrospermum Parkii (Shea) Butter 3%
Argania Spinosa Kernel 0il 1%

Tocopherol 1%
Centella Asiatica Extract 1%
Theobroma Cacao (Cocoa) Seed Butter 1%

Purpose

Moisturise

INDICATIONS& USAGE

Suitable for all types of skin damage due to stretching of the skin. Apply all over skin,concentrating on stretch mark prone areas such as tummy, hips, thighs and bust. Massage liberally into skin twice daily.

KEEP OUT OF REACH OF CHILDREN

lf swallowed, get medical help or contact a Poison Control Center right away.

CAUTION

Skin sensitivity heightens during pregnancy. We advise testing this and all skin care products on a small area, such as the inner forearm,48 hours before first use. Do not use if signs of irritation or rash appear. After using the product, if irritation or rash appears, discontinue use. lf irritation or rash persists, consult your doctor.

DOSAGE

Approximately 0.2-0.4 oz each time.

WARNINGS

For external use only. Keep out ofreach of children.Avoid contact with eyes.

DESCRIPTION

Made with Natural Vitamin E (Tocopherol)

Inactive Ingredients

Water(Aqua),Glycerin, Butylene Glycol,Caprylic/capric Triglyceride,Cetearyl Glucoside,Sorbitan Olivate, Dimethicone,Cetearyl Alcohol,
GlycerylStearate,Hydroxyacetophenone,1,2-hexanediol, Carbomer,,Arginine,Sodium Hyaluronate,Soluble Collagen, Hydrolyzed Elastin,TheobromaCacao (Cocoa) Extract, Cocos Nucifera(Coconut) Oil, Prunus Amygdalus Dulcis(Sweet Almond) Oil,
Fragrance(Parfum),Betula Alba Bark Extract,Boswellia Serrata Extract,Polygonum Cuspidatum RootExtract,Sodium Ascorbate,
Xanthophylls

Manufacturer

Guangzhou Senmai Biotechnology Co.

Address

20-1second floor, 20-2 first to third floor,Dashan Road,Qinghu,Junhe Street, Baiyun district, Guangzhou City, China.

Capacity

300ml/10.1 Fl.oz

Shelf Life

3 Years

Place of Origin

Made in China